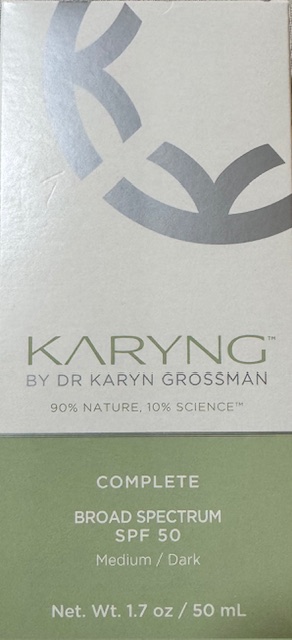 DRUG LABEL: KARYNG Complete SPF Sunscreen
NDC: 85321-002 | Form: CREAM
Manufacturer: Karyng LLC
Category: otc | Type: HUMAN OTC DRUG LABEL
Date: 20250422

ACTIVE INGREDIENTS: TITANIUM DIOXIDE 5.75 g/100 g; ZINC OXIDE 14.5 g/100 g
INACTIVE INGREDIENTS: PENTYLENE GLYCOL; CAPRYLHYDROXAMIC ACID; WATER; DICAPRYLYL CARBONATE; GLYCERIN; STEARETH-21; STEARIC ACID; PROPANEDIOL; CITRUS GRANDIS (GRAPEFRUIT) PEEL OIL; CETEARYL GLUCOSIDE; SODIUM STEAROYL GLUTAMATE; TRIETHOXYCAPRYLYLSILANE; STEARETH-2; CETEARYL ALCOHOL; ISOPROPYL PALMITATE; ECHINACEA PURPUREA; XANTHAN GUM; CAPRYLIC/CAPRIC TRIGLYCERIDE; SILICA; POLYHYDROXYSTEARIC ACID (2300 MW); DIPOTASSIUM GLYCYRRHIZATE; SODIUM C14-16 OLEFIN SULFONATE; CAPRYLYL GLYCOL; TRISODIUM ETHYLENEDIAMINE DISUCCINATE; ALUMINA

KARYNG Complete Broad Spectrum SPF 50 (Medium/Dark)

Active Ingredients

Titanium Dioxide 5.75%

Zinc Oxide 14.5%

Uses

Sunscreen

Warnings

For external use only

When using this product

Keep out of eyes. Rinse with water to remove.

Stop use and ask a doctor if

Rash occurs

Directions

Apply liberally 15 minutes before sun exposure

Reapply at least every 2 hours

Use a water resistant sunscreen if swimming or sweating

Sun protection measures spending time in the sun increases your risk of skin cancer and early skin aging. To decrease this risk, regularly use a sunscreen with a Broad Spectrum SPF value of 15 or higher and other sun protection measures including:

Limit time in the sun, especially from 10am - 2 pm

Wear long sleeved shirts, pants, hats and sunglasses

Childern under 6 months

Ask a doctor

Keep out of reach of children

If swallowed, get medical help or contact Poison Control Center right away. Protect the product in this container from excessive heat and direct sun.

Inactive ingredients

Water, Caprylic/Capric Triglyceride, Dicaprylyl Carbonate, Glycerin, Steareth-2, Pentylene Glycol, Silica, Steareth-21, Polyhydroxystearic Acid, Cetearyl Alcohol, Echinacea Purpurea Extract, Swertia Chirata Leaf Extract, Citrus Grandis (Grapefruit) Peel Oil, Litsea Cubeba Oil,Copper Lysinate/Prolinate, Dipotassium Glycyrrhizate, Sodium Stearoyl Glutamate, Stearic Acid, Propanediol, Cetearyl Glucoside, Methylglucoside Phosphate, Lecithin, Triethoxycaprylylsilane, Isopropyl Palmitate, Sodium C14-16 Olefin Sulfonate, Trisodium Ethylenediamine Disuccinate, Alumina, Xanthan Gum, Caprylhydroxamic Acid, Caprylyl Glycol, Iron Oxides (CI 77491), Iron Oxides (CI 77492), Iron Oxides (CI 77499).

INDICATIONS AND USAGE

Helps prevent sunburn

If used as directed with other sun protection measures (see Directions), decreases the risk of skin cancer and early skin aging caused by sun.